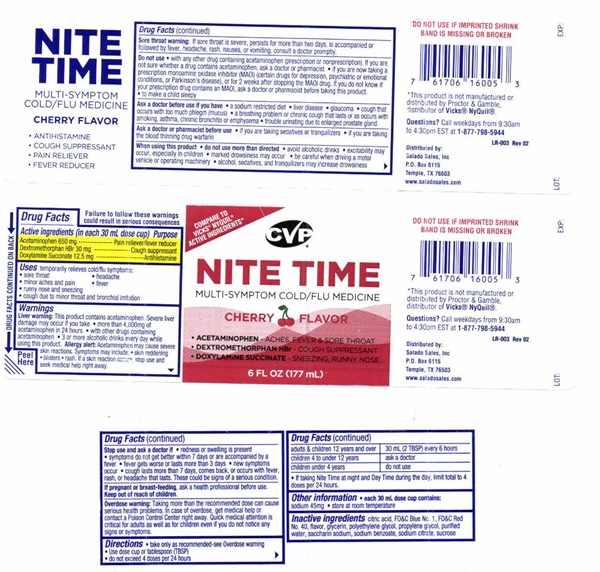 DRUG LABEL: Nite-TimeCOLD/FLU CHERRY
NDC: 57243-502 | Form: LIQUID
Manufacturer: Salado Sales, Inc.
Category: otc | Type: HUMAN OTC DRUG LABEL
Date: 20231229

ACTIVE INGREDIENTS: ACETAMINOPHEN 650 mg/30 mL; DEXTROMETHORPHAN HYDROBROMIDE 30 mg/30 mL; DOXYLAMINE SUCCINATE 12.5 mg/30 mL
INACTIVE INGREDIENTS: CITRIC ACID MONOHYDRATE; FD&C BLUE NO. 1; FD&C RED NO. 40; GLYCERIN; POLYETHYLENE GLYCOL 400; WATER; SACCHARIN SODIUM; SODIUM BENZOATE; SODIUM CITRATE; SUCROSE

Night Time Cherry 502

Drug FactsActive ingredients (in each 30 mL dose cup)

Acetaminophen 650 mg
Dextromethorphan HBr 30 mg
Doxylamine Succinate 12.5 mg

Purpose

Pain reliever/fever reducer
Cough suppressant
Antihistamine

Keep Out Of Reach Of Children

Uses

temporarily relieves cold/flu symptoms:

- sore throat
- minor aches and pain
- runny nose and sneezing
- cough due to minor sore throat and bronchial irritation
- headache
- fever

Warnings

Failure to follow these warnings could result in serious consequences
Liver warning: This product contains acetaminophen. Severe liver damage may occur if you take

- more than 4,000 mg of acetaminophen in 24 hours
- with other drugs containing acetaminophen
- 3 or more alcoholic drinks every day while using this product.

Allergy alert:

Acetaminophen may cause severe skin reactions. Symptoms may include

- skin reddening
- blisters
- rash.

If a skin reaction occurs, stop use and seek medical help right away

Sore throat warning: If sore throat is severe, persists for more than 2 days, is accompanied or followed by fever, headache, rash, nausea, or vomiting, consult a doctor promptly.

Do not use

- with any other drug containing acetaminophen (prescription or nonprescription) If you are not sure whether a drug contains acetaminophen, ask a doctor or pharmacist
- if you are now taking a prescription monoamine oxidase inhibitor (MAOI) (certain drugs for depression,psychiatric or emotional conditions, or Parkinson's disease), or for 2 weeks after stopping the MAOI drug. If you do not know if your prescription drug contains an MAOI, ask a doctor or pharmacist before taking this product
- to make a child sleepy

Ask a doctor before use if you have

- a sodium restricted diet
- liver disease
- glaucoma
- cough that occurs with too much phlegm (mucus)
- a breathing problem or chronic cough that lasts or as occurs with smoking, asthma, chronic bronchitis or emphysema
- trouble urinating due to enlarged prostate gland

Ask a doctor or pharmacist before use

- if you are taking sedatives or tranquilizers
- if you are taking the blood thinning drug warfarin

When using this product

- do not use more than directed
- avoid alcoholic drinks
- excitability may occur, especially in children
- marked drowsiness may occur
- be careful when driving a motor vehicle or operating machinery
- alcohol, sedatives, and tranquilizers may increase drowsiness

Stop use and ask a doctor if

- redness or swelling is present
- symptoms do not get better within 7 days or are accompanied by a fever
- fever gets worse or lasts more than 3 days
- new symptoms occur
- cough lasts more than 7 days, comes back, or occurs with fever, rash, headache that lasts

These could be signs of a serious condition.

Pregnant Or Breast-Feeding

ask a health professional before use.

Overdose warning

Taking more than the recommended dose can cause serious health problems. In case of overdose, get medical help or contact a Poison Control Center right away. Quick medical attention is critical for adults as well as for children even if you do not notice any signs or symptoms.

Directions

- take only as recommended-see Overdose warnings
- Use dose cup or tablespoon (TBSP)
- do not exceed 4 doses per 24 hours

adults & children 12 years and over 30 mL (2 TBSP) every 6 hours

children 4 to under 12 years ask a doctor

children under 4 years do not use

- If taking Nite Time at night and Day Time during the day, limit total to 4 doses per 24 hours

Other Information

- each 30 mL dose cup contains:
- sodium 45 mg
- store at room temperature

Inactive ingredients

citric acid, FD and C Blue No. 1, FD&C Red No. 40, flavor, glycerin, polyethylene glycol, propylene glycol, purified water, saccharin sodium, sodium benzoate, sodium citrate, sucrose

Nite Time Cherry product label

Compare to VICKS® NYQUIL® active ingredients

CVP® CONSUMER VALUE PRODUCTS
Nite-Time COLD/FLU Medicine
Multi-Symptom CHERRY FLAVOR
Acetaminophen • Aches, Fever & Sore Throat
Dextromethorphan • Cough
Doxylamine Succinate • Sneezing, Runny nose
6 FL OZ (177 mL)
DO NOT USE IF IMPRINTED SHRINK BAND IS MISSING OR BROKEN
*This product is not manufactured or distributed by Proctor and Gamble, distributor of Vicks® Nyquil® LR-003
Questions? Call weekdays from 9:30am to 4:30pm EST 1-877-795-5944

LR-003 Rev 02
Distributed by:
Salado Sales, Inc.
P.O. Box 6115 Temple, TX 76503
www.saladosales.com
LOT: EXP:
Peel Here DRUG FACTS CONTINUED ON BACK
CHERRY FLAVOR Nite-Time Multi-Symptom COLD/FLU Medicine

- Antihistamine
- Cough Suppressant
- Pain Reliever
- Fever Reducer

res